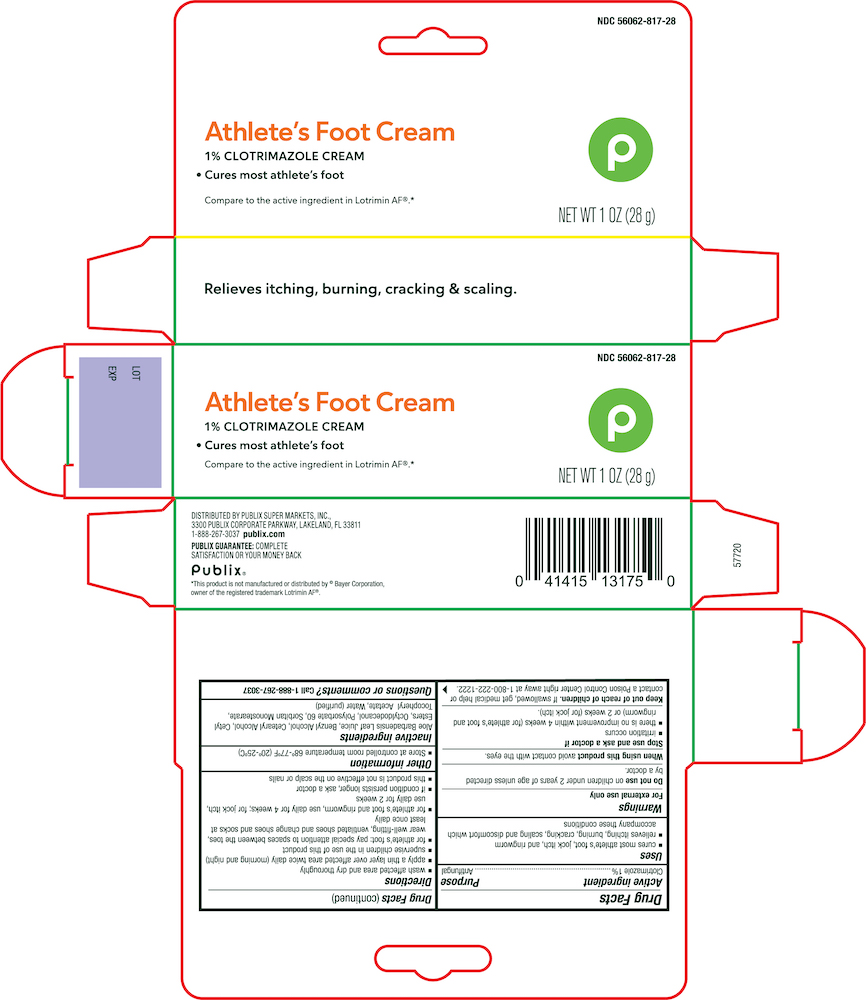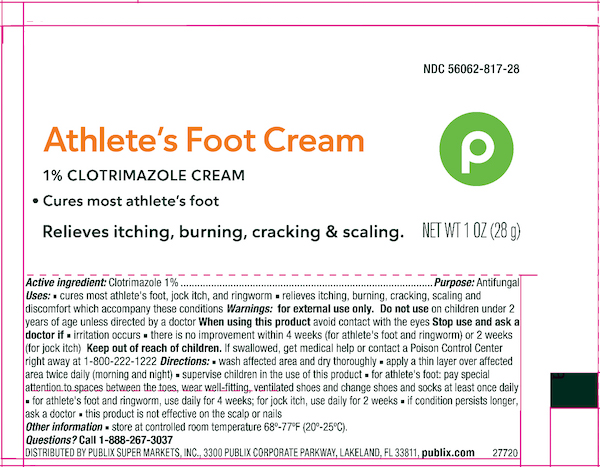 DRUG LABEL: Publix Athletic Foot
NDC: 56062-817 | Form: CREAM
Manufacturer: PUBLIX SUPER MARKETS, INC.
Category: otc | Type: HUMAN OTC DRUG LABEL
Date: 20240802

ACTIVE INGREDIENTS: CLOTRIMAZOLE 10 mg/1 g
INACTIVE INGREDIENTS: ALOE VERA LEAF; BENZYL ALCOHOL; CETOSTEARYL ALCOHOL; CETYL ESTERS WAX; OCTYLDODECANOL; POLYSORBATE 60; SORBITAN MONOSTEARATE; .ALPHA.-TOCOPHEROL ACETATE; WATER

Active ingredient

Clotrimazole 1%

Purpose

Antifungal

Uses

- Cures most athlete's foot, jock itch and ringworm
- Relieves the itching, burning, scaling, chafing and discomfort associated with these conditions

Warnings For external use only

Do not use on children under 2 years of age unless directed by a doctor.

When using this product avoid contact with eyes.

Stop use and consult a doctor if

- irritation occurs
- if there is not improvement within 2 weeks

Keep out of the reach of children

if swallowed, get medical help or contact a poison control center right away.

Directions

- Wash the affected area and dry thoroughly.
- Apply a thin layer of this product over affected area twice daily (morning and night)
- Supervise children in the use of this product.
- use daily for 2 weeks.
- If conditions persist longer, consult a doctor.
- This product is not effective on the scalp or nails.

Other information

- Store at controlled room temperature 20°-25°C (68°-77°F).
- Close cap tightly after use.

Inactive ingredients

Aloe Barbadensis Leaf Juice, Benzyl Alcohol, Cetearyl Alcohol, Cetyl Esters, Octyldodecanol, Polysorbate 60, Sorbitan Monostearate, Tocopheryl Acetate, Water (purified).

Principal Display Panel

Publix Athletes Foot Cream NDC# 56062-817-28

1% Clotrimazole Cream

Cures Most athlete's foot

NET WT 1 OZ (28g)